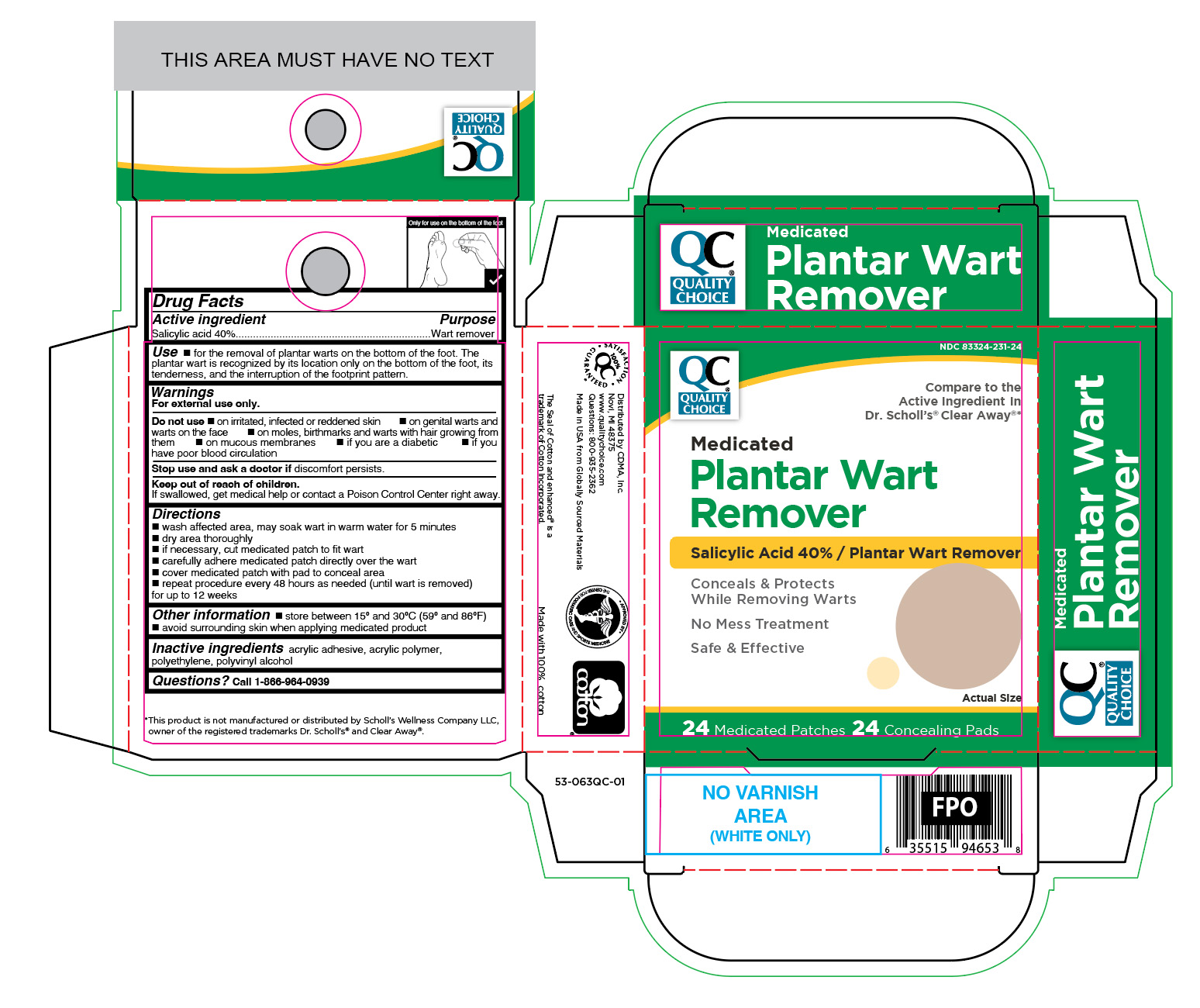 DRUG LABEL: Salicylic Acid
NDC: 83324-231 | Form: PATCH
Manufacturer: Chain Drug Marketing Association
Category: otc | Type: HUMAN OTC DRUG LABEL
Date: 20260102

ACTIVE INGREDIENTS: SALICYLIC ACID 400 mg/1 g
INACTIVE INGREDIENTS: POLYVINYL ALCOHOL; HIGH DENSITY POLYETHYLENE

Quality Choice Medicated Plantar Wart Remover

Active ingredient

Salicylic acid 40%

Purpose

Wart remover

Uses

- for the removal of plantar warts on the bottom of the foot. The plantar wart is recognized by its location only on the bottom of the foot, its tenderness, and the interruption of the footprint pattern.

Warnings

For external use only.

Do not use

- on irritated, infected or reddened skin
- on genital warts and warts on the face
- on moles, birthmarks and warts with hair growing from them
- on mucous membranes
- if you are diabetic
- if you have poor blood circulation

Stop use and ask a doctor if

discomfort persists

Keep out of reach of children.

If swallowed, get medical help or contact a Poison Control Center right away.

Directions

- wash affected area, may soak wart in warm water for 5 minutes
- dry area thoroughly
- if necessary, cut medicated patch to fit wart
- carefully adhere medicated patch directly over the wart
- cover medicated patch with pad to conceal area
- repeat procedure every 48 hours as needed (until wart is removed) for up to 12 weeks

Other information

- store between 15° and 30°C (59° and 86°F)
- avoid surrounding skin when applying medicated product

Inactive ingredients

acrylic adhesive, acrylic polymer, polyethylene, polyvinyl alcohol

Questions?

call 1-866-964-0939

RECENT MAJOR CHANGES

.

Principal Display Panel

QC

Quality Choice

Medicated

Plantar Wart
Remover

Salicylic Acid 40% / Plantar Wart Remover

Conceals & Protects

While Removing Warts

No Mess Treatment

Safe & Effective

24 Medicated Patches 24 Concealing Pads